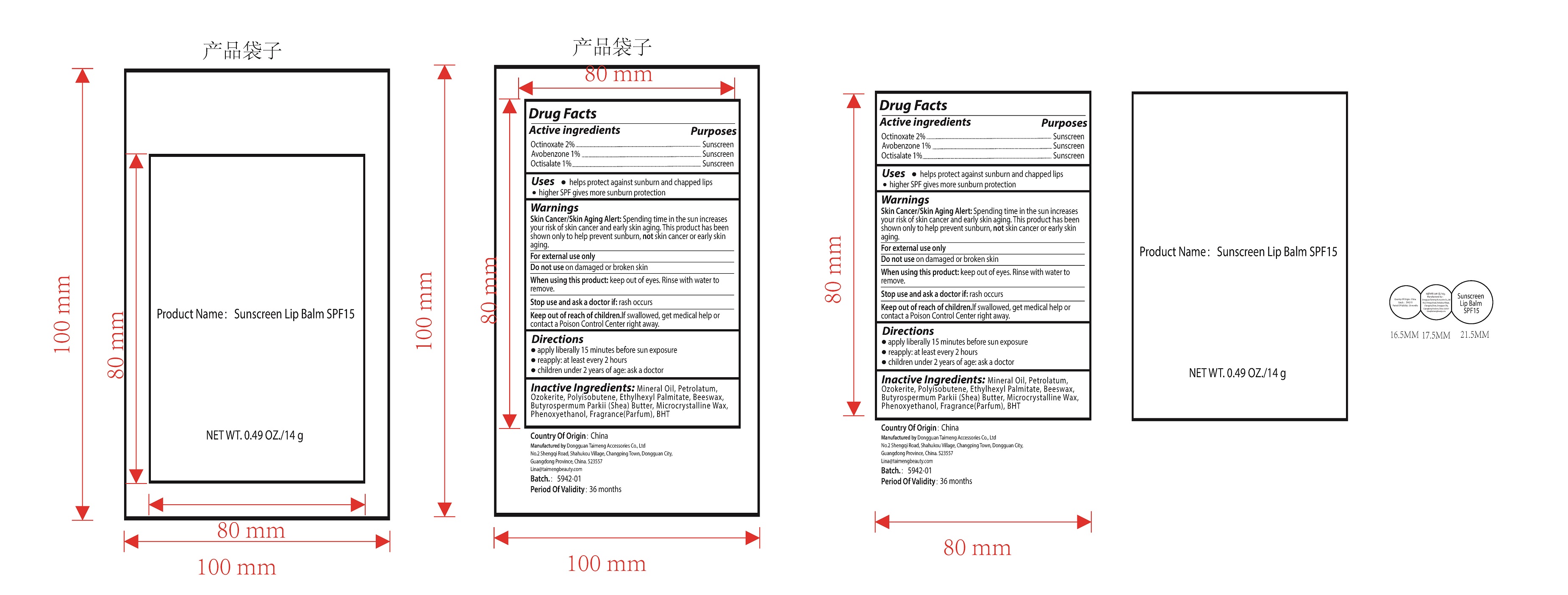 DRUG LABEL: Sunscreen Lip Balm SPF15
NDC: 87353-001 | Form: LIPSTICK
Manufacturer: Dongguan Taimeng Accessories  Co., Ltd.
Category: otc | Type: HUMAN OTC DRUG LABEL
Date: 20260122

ACTIVE INGREDIENTS: OCTINOXATE 2 g/100 g; AVOBENZONE 1 g/100 g; OCTISALATE 1 g/100 g
INACTIVE INGREDIENTS: MICROCRYSTALLINE WAX; BHT; ETHYLHEXYL PALMITATE; CERESIN; BEESWAX; POLYISOBUTYLENE (1000 MW); PHENOXYETHANOL; BUTYROSPERMUM PARKII (SHEA) BUTTER

87353-001

Active ingredient

Octinoxate 2%,Avobenzone 1%,Octisalate 1%

Purpose

Sunscreen

Uses

- helps protect against sunbumn and chapped lips

- higher SPF gives more sunburn protection

Warnings

1. Skin Cancer/Skin Aging Alert: Spending time in the sun increasesyour risk of skin cancer and early skin aging. This product has been shown only to help prevent sunburn, not skin cancer or early skinaging.

2. For external use only

Do not use

on damaged or broken skin

When using this product

keep out of eyes. Rinse with water toremove.

Stop use and ask a doctor if

rash occurs

Keep out of reach of children.

lf swallowed, get medical help orcontact a Poison Control Center right away.

Directions

apply liberally 15 minutes before sun exposure

reapply: at least every 2 hours

children under 2 years of age: ask a doctor

Inactive ingredients

Ozokerite, Polyisobutene,Ethylhexyl Palmitate, Beeswax, Butyrospermum Parkii (Shea)Butter,Microcrystalline Wax, Phenoxyethanol, Fragrance(Parfum),BHT